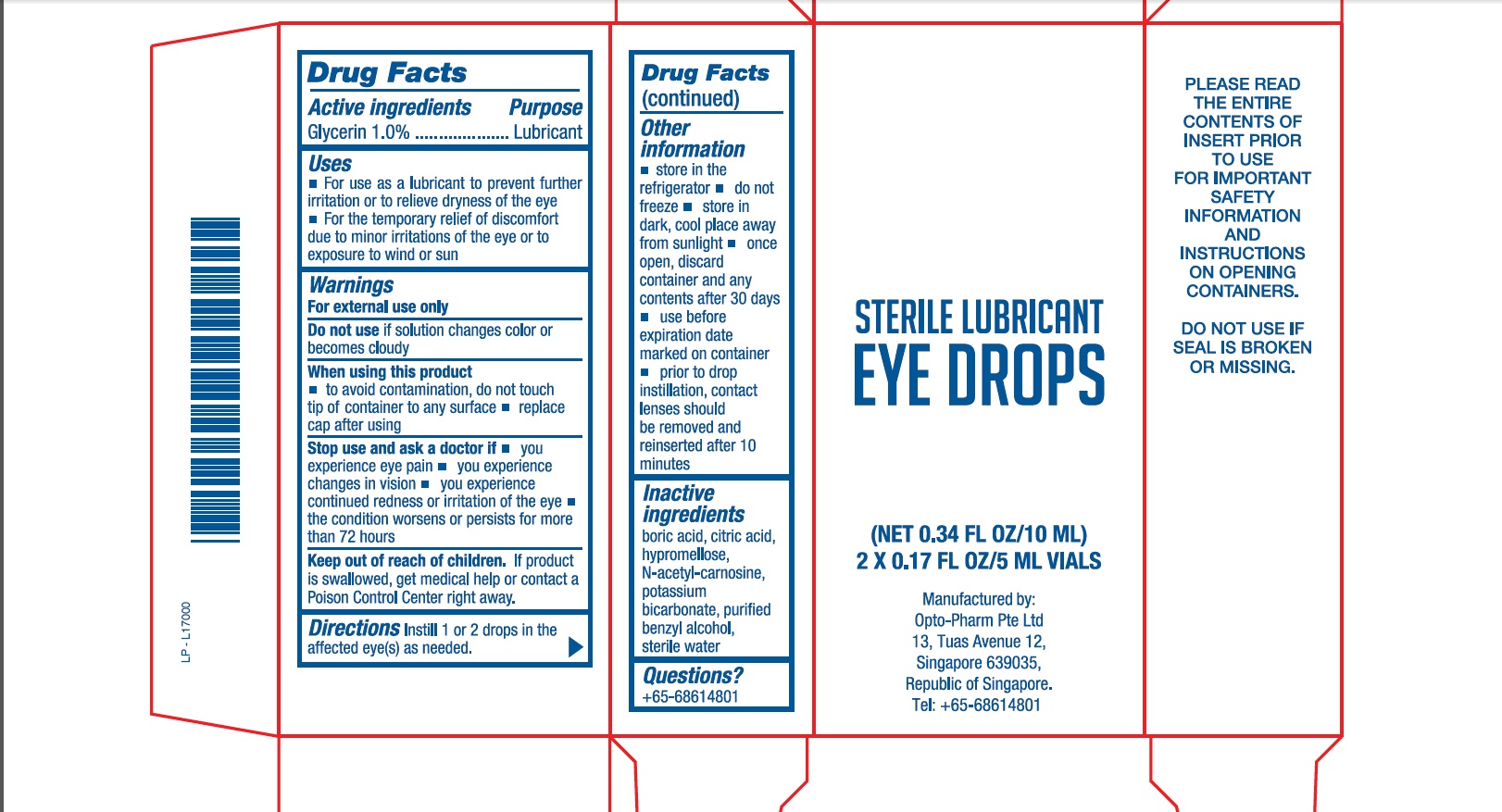 DRUG LABEL: Eye Drops
NDC: 46823-001 | Form: SOLUTION
Manufacturer: Opto-Pharm Pte Ltd
Category: otc | Type: HUMAN OTC DRUG LABEL
Date: 20170306

ACTIVE INGREDIENTS: GLYCERIN 1 g/100 g
INACTIVE INGREDIENTS: BORIC ACID; CITRIC ACID MONOHYDRATE; HYPROMELLOSE, UNSPECIFIED; N-ACETYLCARNOSINE; POTASSIUM BICARBONATE; BENZYL ALCOHOL; WATER

Drug Facts

Active Ingredient

Glycerin.....1.0%

Purpose

Lubricant

Uses

- For use as a lubricant to prevent further irritation or to relieve dryness of the eye
- for the temporary relief of discomfort due to minor irritations of the eye or to exposure to wind or sun

Warnings

For external use only

Do not use if

solution changes color or becomes cloudy

When using this product

- to avoid contamination, do not touch tip of container to any surface
- replace cap after using

Stop use and ask a doctor if

- you experience eye pain
- you experience changes in vision
- you experience continued redness or irritation of the eye
- the condition worsens or persists for more than 72 hours

Keep out of reach of children

If product is swallowed, get medical help or contact a Poison Control Center right away.

Directions

Instill 1 or 2 drops in the affected eye(s) as needed

Other informations

- store in the refrigerator
- do not freeze
- store in dark, cool place away from sunlight
- once open, discard container and any contents after 30 days
- use before expiration date marked on container
- prior to drop instillation, contact lenses should be removed and reinserted after 10 minutes

Inactive ingredients

boric acid, citric acid, hypromellose, N-acetyl-carnosine, potassium bicarbonate, purified benzyl alcohol, sterile water

Questions

+65-68614801

Principal Display Panel

NDC 46823-001-05

STERILE LUBRICANT EYE DROPS

2X0.17 fl oz/5 ml vials

(Net 0.34 fl oz/10 ml)